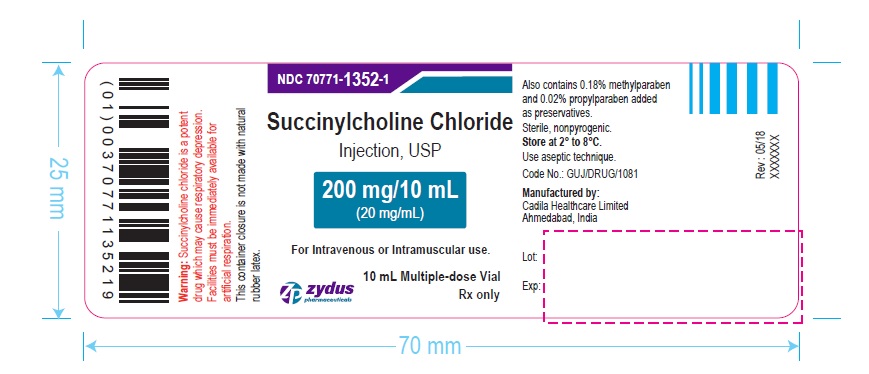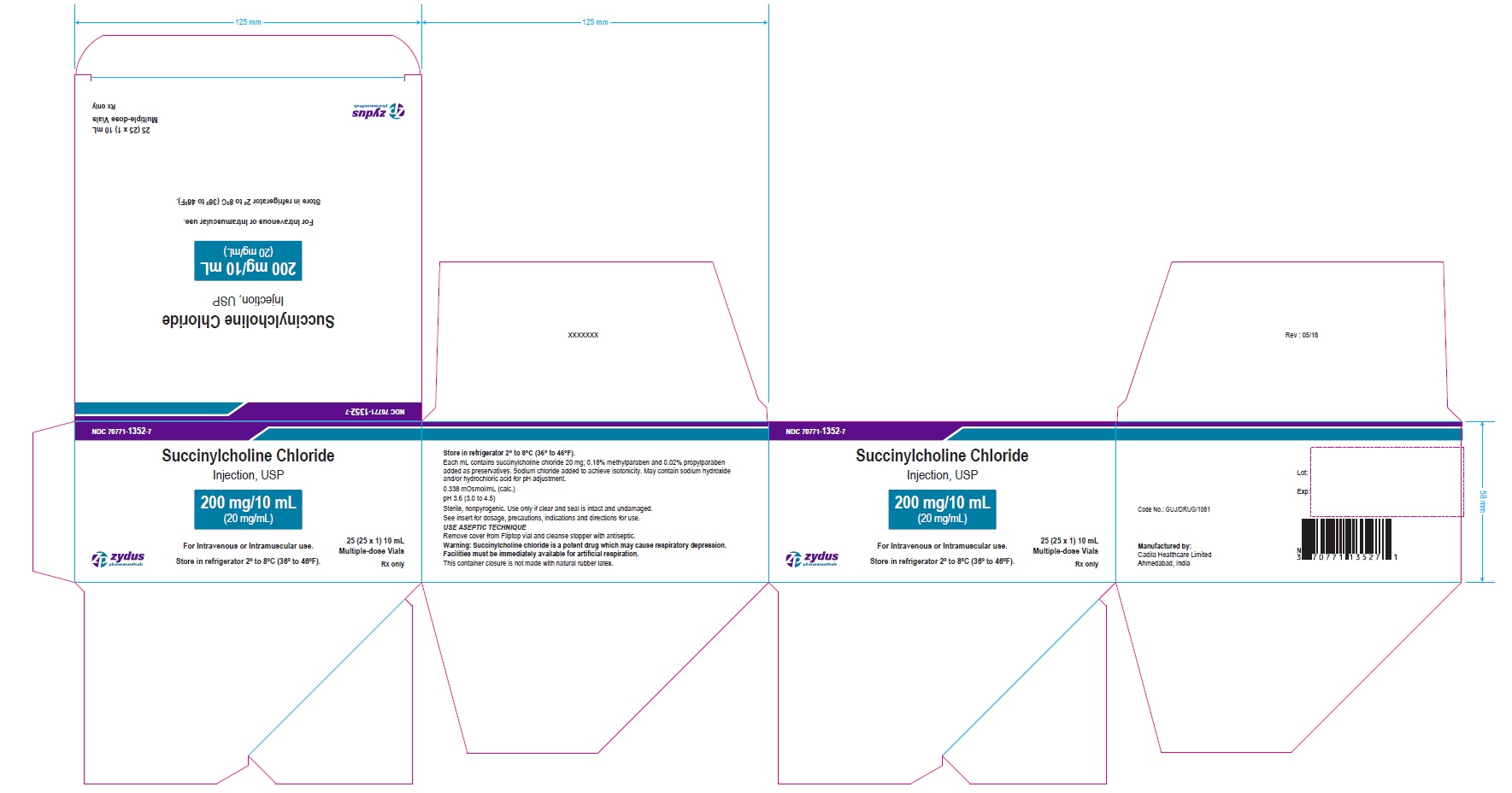 DRUG LABEL: Succinylcholine Chloride
NDC: 70771-1352 | Form: INJECTION, SOLUTION
Manufacturer: Zydus Lifesciences Limited
Category: prescription | Type: HUMAN PRESCRIPTION DRUG LABEL
Date: 20231019

ACTIVE INGREDIENTS: SUCCINYLCHOLINE CHLORIDE 20 mg/1 mL
INACTIVE INGREDIENTS: HYDROCHLORIC ACID; METHYLPARABEN 1.8 mg/1 mL; PROPYLPARABEN 0.2 mg/1 mL; SODIUM CHLORIDE; SODIUM HYDROXIDE

Succinylcholine Chloride Injection, USP

PACKAGE LABEL.PRINCIPAL DISPLAY PANEL

Vial Label

NDC 70771-1352-1

Succinylcholine Chloride Injection, USP

200 mg/10 mL (20 mg/mL)

For Intravenous or Intramuscular use.

10 mL Multiple-dose Vial

Rx only

Zydus Pharmaceuticals

PACKAGE LABEL.PRINCIPAL DISPLAY PANEL

Carton Label

NDC 70771-1352-7

Succinylcholine Chloride Injection, USP

200 mg/10 mL (20 mg/mL)

For Intravenous or Intramuscular use.

Store in refrigerator 2º to 8ºC (36º to 46ºF).

25 (25 x 1) 10 mL Multiple-dose Vial

Rx only

Zydus Pharmaceuticals